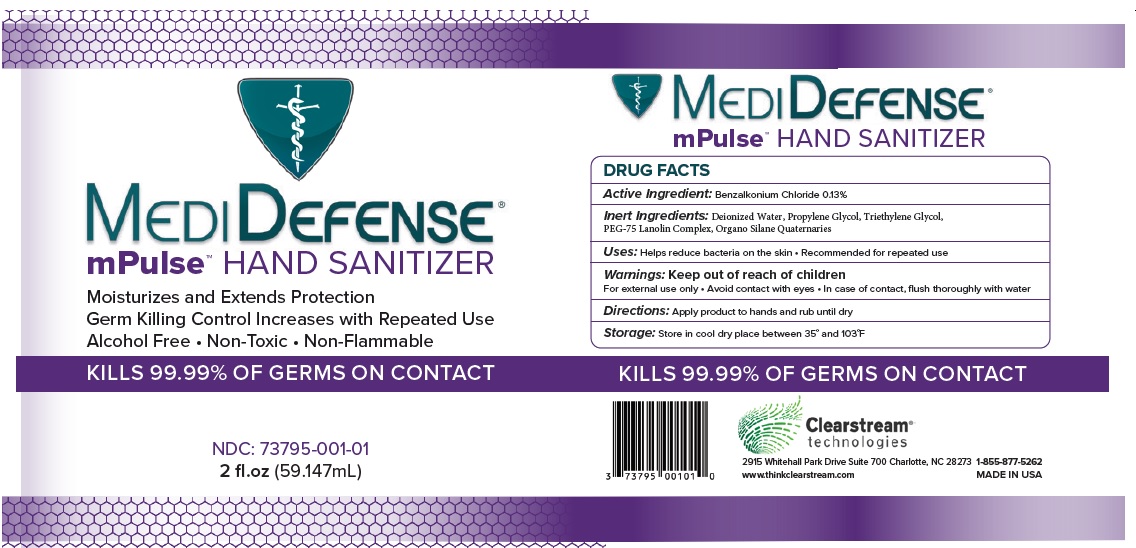 DRUG LABEL: Medi Defense mPulse Hand Sanitizer
NDC: 73795-001 | Form: SPRAY
Manufacturer: CLEARSTREAM TECHNOLOGIES, LLC
Category: otc | Type: HUMAN OTC DRUG LABEL
Date: 20230523

ACTIVE INGREDIENTS: BENZALKONIUM CHLORIDE 1.3 mg/1 mL
INACTIVE INGREDIENTS: DIMETHYLOCTADECYL(3-(TRIMETHOXYSILYL)PROPYL)AMMONIUM CHLORIDE; PROPYLENE GLYCOL; TRIETHYLENE GLYCOL; PEG-75 LANOLIN; WATER

Medi Defense mPulse Hand Sanitizer

Active ingredient

Benzalkonium Chloride 0.13%

Purpose

Antimicrobial

Uses

Help reduce bacteria on the skin.

Recommended for repeated use

Warnings

For external use only.

Avoid contact with eyes. In case of eye contact flush thoroughly with water.

Directions

- Apply product to hands and rub until dry.

Storage

Store in cool dry place between 35^0 and 103^0F

Inactive ingredients

Deionized Water, Propylene glycol, Triethylene glycol, PEG-75 Lanolin complex, Organo Silane Quaternaries